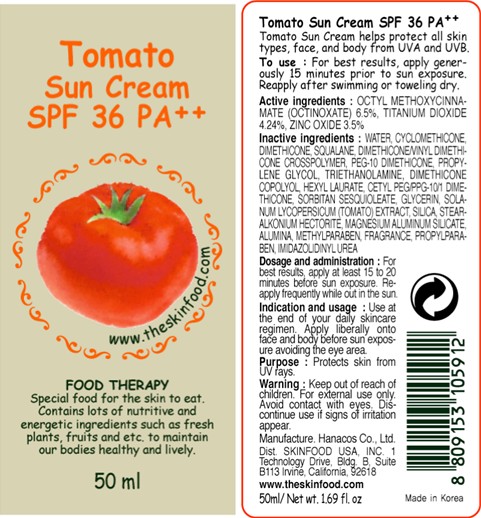 DRUG LABEL: TOMATO SUN
NDC: 76214-035 | Form: CREAM
Manufacturer: SKINFOOD CO., LTD.
Category: otc | Type: HUMAN OTC DRUG LABEL
Date: 20111007

ACTIVE INGREDIENTS: OCTINOXATE 3.25 mL/50 mL; TITANIUM DIOXIDE 2.12 mL/50 mL; ZINC OXIDE 1.75 mL/50 mL
INACTIVE INGREDIENTS: WATER; CYCLOMETHICONE; SQUALANE; PROPYLENE GLYCOL; DIMETHICONE; TROLAMINE; HEXYL LAURATE; SORBITAN SESQUIOLEATE; GLYCERIN; TOMATO; MAGNESIUM ALUMINUM SILICATE; SILICON DIOXIDE; ALUMINUM OXIDE; METHYLPARABEN; PROPYLPARABEN; IMIDUREA

Drug Facts

ACTIVE INGREDIENT

Active ingredients: OCTINOXATE 6.5%, Titanium Dioxide 4.24%, Zinc Oxide 3.5%

Inactive ingredients:
Water, Cyclomethicone, Dimethicone, Squalane, Dimethicone/Vinyl Dimethicone Crosspolymer, PEG-10 Dimethicone, Propylene Glycol, Triethanolamine, Dimethicone Copolyol, Hexyl Laurate, Cetyl Peg/Ppg-10/1 Dimethicone, Sorbitan Sesquioleate, Glycerin, Solanum Lycopersicum (Tomato) Extract, Silica, Stearalkonium Hectorite, Magnesium Aluminum Silicate, Alumina, Methylparaben, Fragrance, Propylparaben, Imidazolidinyl Urea

Purpose: Protects skin from UV rays.

Warnings:
For external use only.
Avoid contact with eyes.
Discontinue use if signs of irritation appear.

Keep out of reach of children:
Keep out of reach of children.

Indication and usage:
Use at the end of your daily skincare regimen.
Apply liberally onto face and body before sun exposure avoiding the eye area.

Dosage and administration:
For best results, apply at least 15 to 20 minutes before sun exposure.
Reapply frequently while out in the sun.